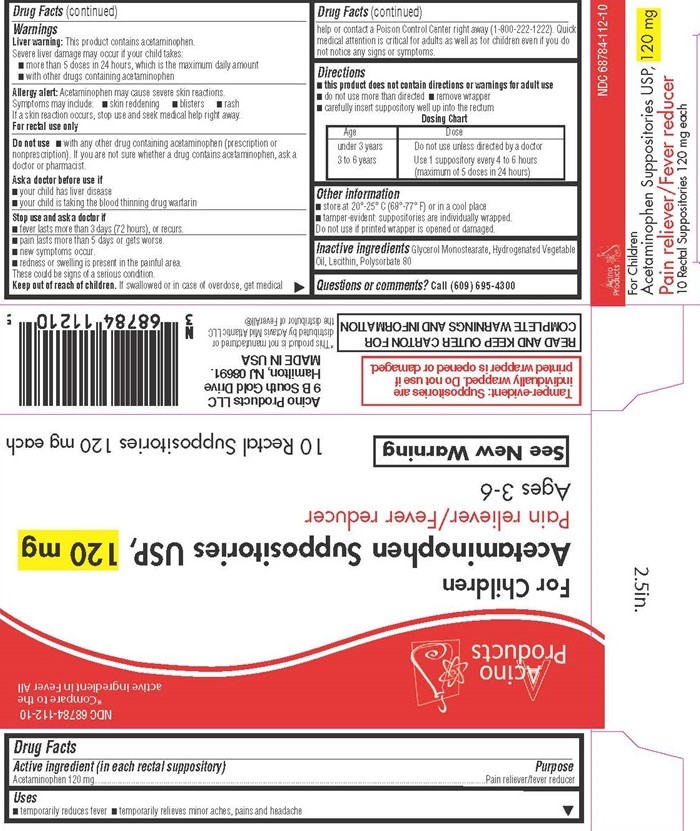 DRUG LABEL: ACETAMINOPHEN
NDC: 68784-112 | Form: SUPPOSITORY
Manufacturer: Acino Products, LLC
Category: otc | Type: HUMAN OTC DRUG LABEL
Date: 20160202

ACTIVE INGREDIENTS: ACETAMINOPHEN 120 mg/1 1
INACTIVE INGREDIENTS: GLYCERYL MONOSTEARATE; FAT, HARD; HYDROGENATED SOYBEAN LECITHIN; POLYSORBATE 80

Acetaminophen Suppositories - 112 DPL

Drug Facts Active ingredient (in each rectal suppository)

Acetaminophen 120 mg

Purpose

Pain reliever/fever reducer

Keep out of reach of children.

If swallowed or in case of overdose, get medical help or contact a Poison Control Center right away (1-800-222-1222) Quick medical attention is critical for adults as well as for children even if you do not notice any signs or symptoms.

Uses

- temporarily reduces fever
- temporarily relieves minor aches, pains and headache

Warnings

Liver warning: This product contains acetaminophen.

Severe liver damage may occur if your child takes:

- more than 5 doses in 24 hours, which is the maximum daily amount
- with other drugs containing acetaminophen

Allergy alert: Acetaminophen may cause severe skin reactions.

Symptoms may include:

- skin reddening
- blisters
- rash

If a skin reaction occurs, stop use and seek medical help right away.

For rectal use only.

Do not use

- with any other drug containing acetaminophen (prescription or nonprescription). If you are not sure whether a drug contains acetaminophen, ask a doctor or pharmacist.

Ask a doctor before use if

- your child has liver disease
- your child is taking the blood thinning drug warfarin

Stop use and ask a doctor if

- fever lasts more than 3 days (72 hours), or recurs.
- pain lasts more than 5 days or gets worse.
- new symptoms occur.
- redness or swelling is present in the painful area.

These could be signs of a serious condition.

Directions

- this product does not contain directions or warnings for adult use
- do not use more than directed
- remove wrapper
- carefully insert suppository well up into the rectum

Dosing Chart

Age | Dose
under 3 years; 3 to 6 years | Do not use unless directed by a doctor; Use 1 suppository every 4 to 6 hours (maximum of 5 doses in 24 hours)

Other information

- store at 20°-25°C (68°-77°F)
- tamper evident suppositories are individually wraped.

Do not use if printed wrapper is open or damaged.

Inactive ingredients

Glycerol Monostearate, Hydrogenated Vegetable Oil, Lecithin, Polysorbate 80

Questions or comments?

Call (609-695-4300)

Acetaminophen Suppositories For Children product label

Acion Products

NDC 68784-112-10

*Compare to the active ingredient in Fever All

For Children

Acetaminophen Suppositories USP, 120 mg

Pain reliever/Fever reducer

Age 3-6

See New Warning

10 Rectal Suppositories 120 mg each

Tamper-evident: Suppositories are individually wrapped. Do not use if printed wrapper is open or damaged

READ AND KEEP OUTER CARTON FOR COMPLETE WARNINGS AND INFORMATION

Acino Products LLC

9B South Gold Drive

Hamilton, NJ 08691.

MADE IN THE USA

*This product is not manufactured or distributed by Acino Mid Atlantic LLC the distributed of Fever All®